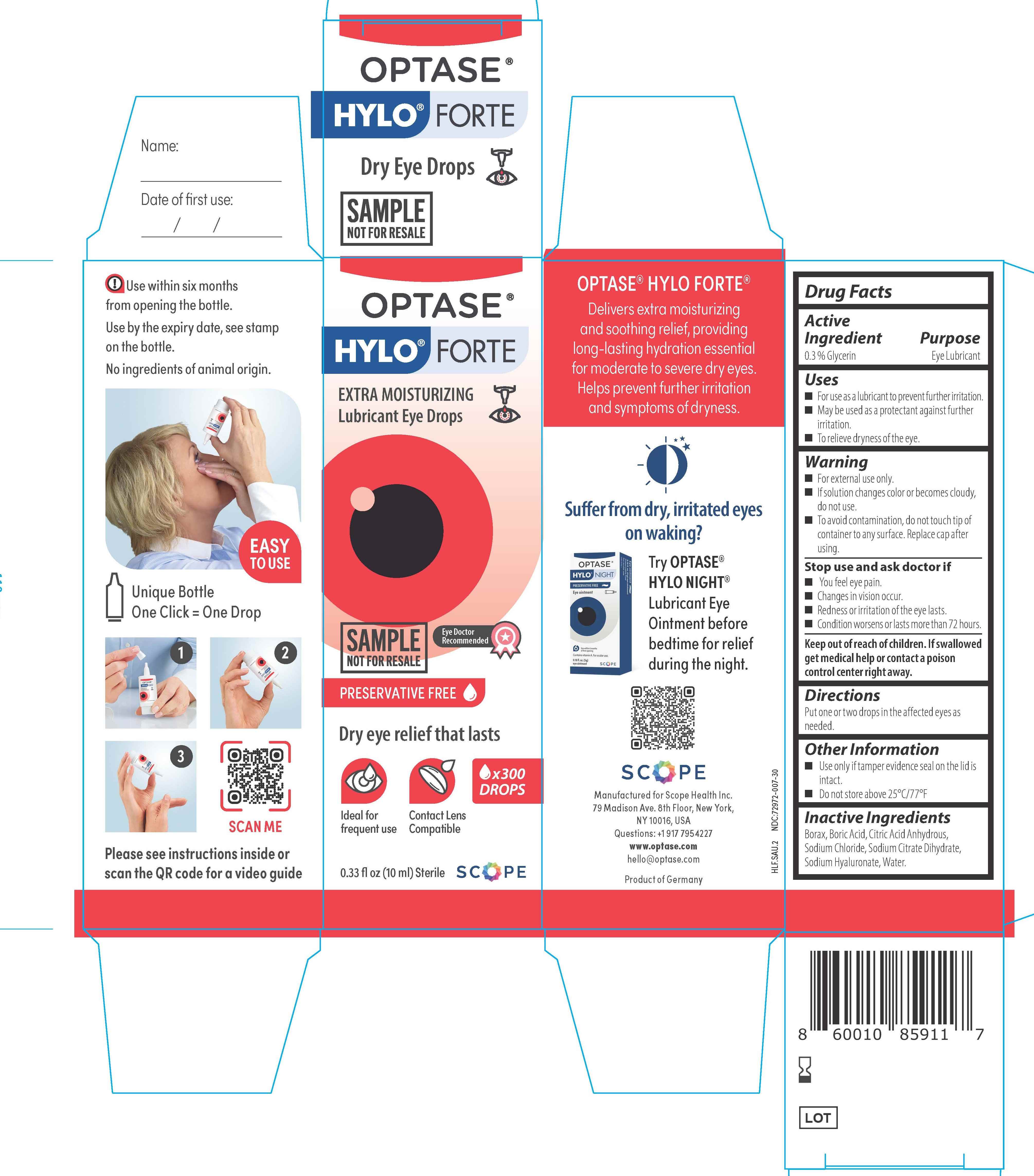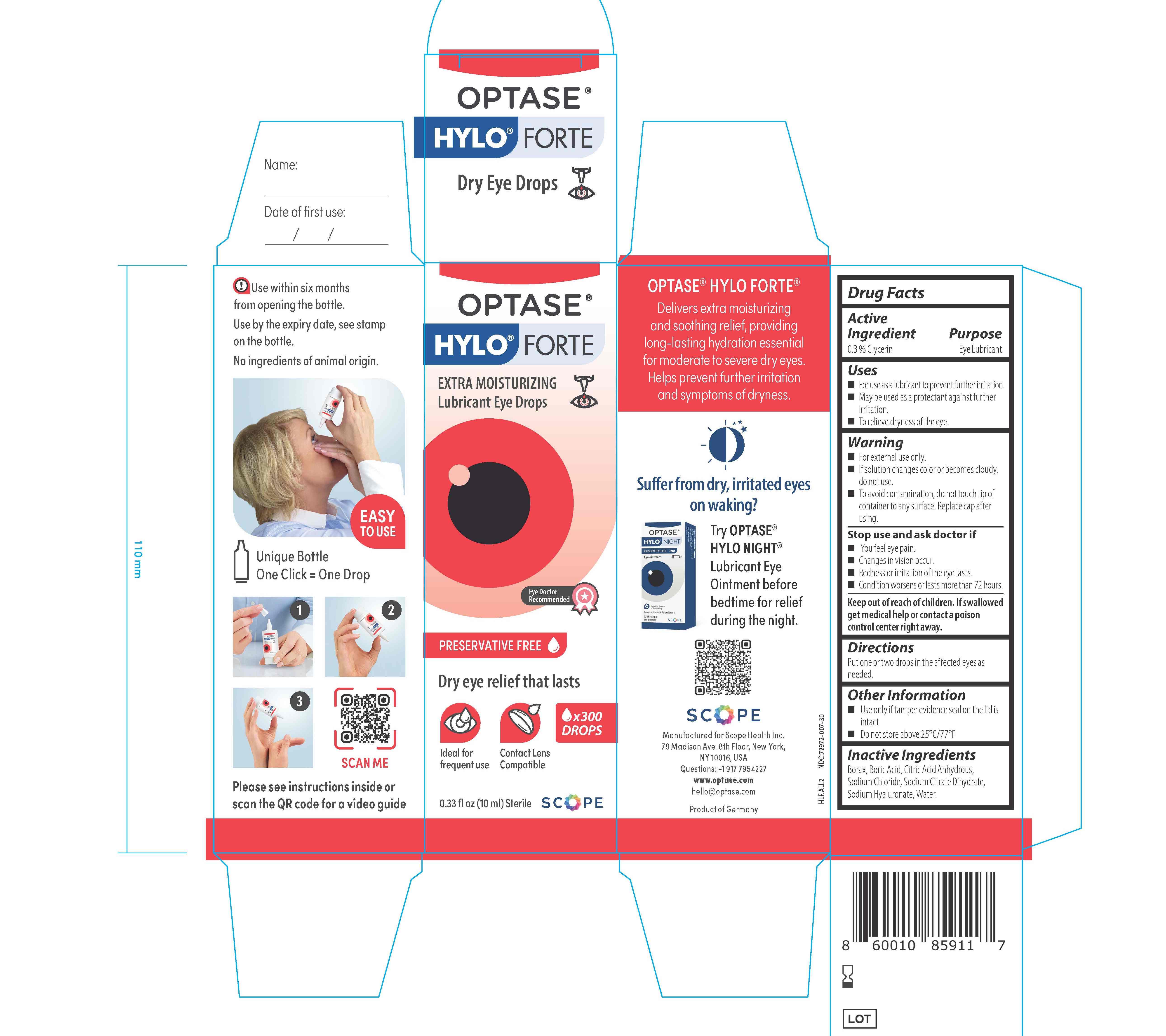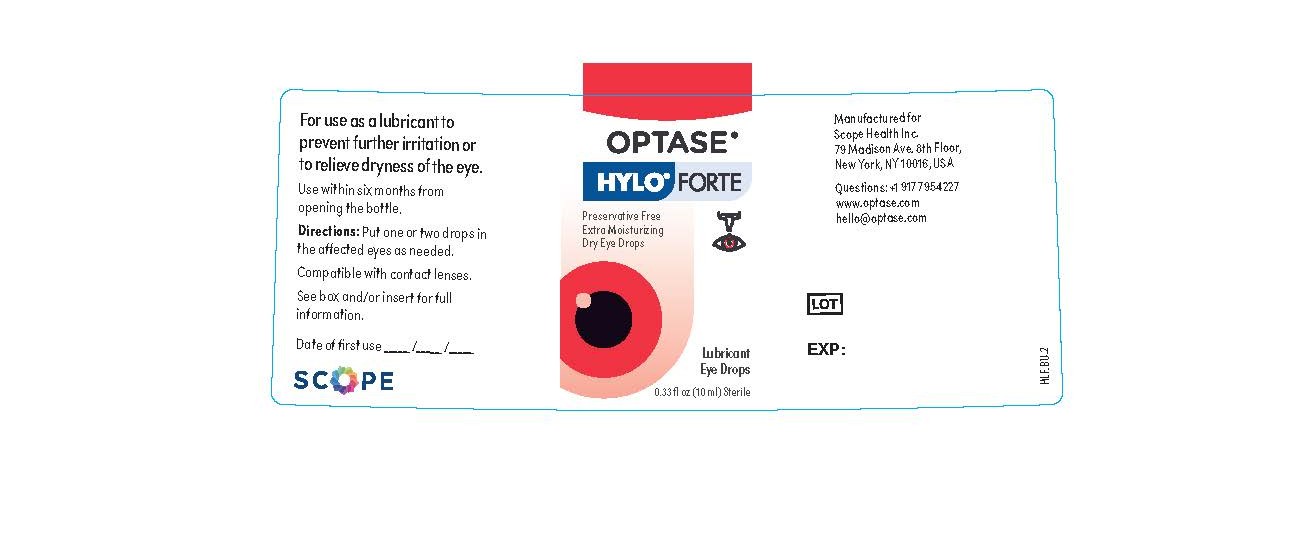 DRUG LABEL: Optase
NDC: 72972-008 | Form: SOLUTION/ DROPS
Manufacturer: Scope Health Inc
Category: otc | Type: HUMAN OTC DRUG LABEL
Date: 20260130

ACTIVE INGREDIENTS: GLYCERIN 0.3 mg/1 mL
INACTIVE INGREDIENTS: SODIUM BORATE; SODIUM CHLORIDE; BORIC ACID; ANHYDROUS CITRIC ACID; HYALURONATE SODIUM; SODIUM CITRATE; WATER

Optase Hylo Forte

Keep out of reach of children.
If swallowed get medical
help or contact a poison
control center right away.

ACTIVE INGREDIENT

0.3 % glycerin

PURPOSE

Eye Lubricant

Inactive Ingredients
Borax, Boric Acid, Citric Acid anhydrous,
Sodium Chloride, Sodium Citrate Dihydrate, Sodium Hyaluronate, water.

Directions:
Put one or two drops in the
affected eyes as needed.

Warning
■ For external use only.
■ If solution changes color or becomes cloudy, do not use.
■ To avoid contamination, do not touch tip of container to any surface. Replace cap after using.
Stop use and ask doctor if
■ You feel eye pain.
■ Changes in vision occur.
■ Redness or irritation of the eye lasts.
■ Condition worsens or lasts more than 72 hours.

Uses
• For use as a lubricant to prevent
further irritation.
• May be used as a protectant against
further irritation.
• To relieve dryness of the eye.